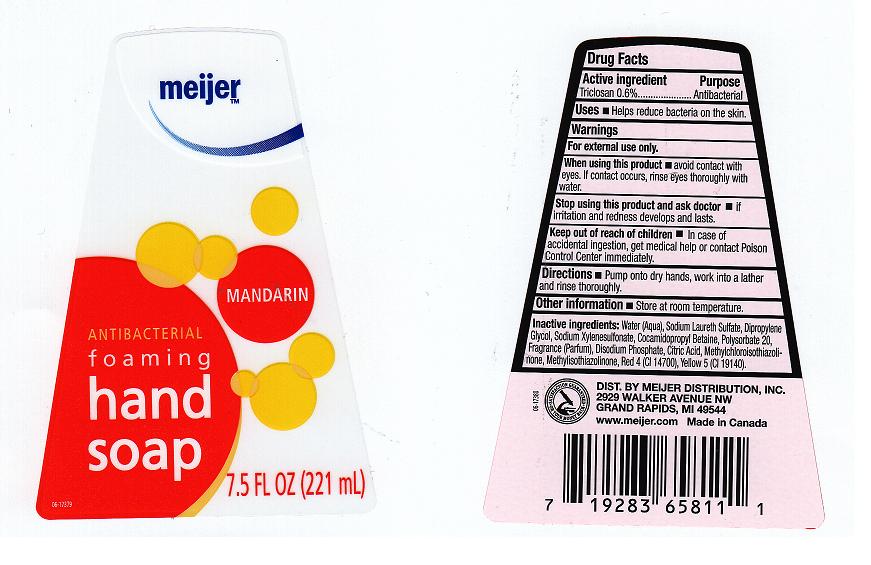 DRUG LABEL: ANTIBACTERIAL FOAMING 
NDC: 41250-185 | Form: LIQUID
Manufacturer: MEIJER DISTRIBUTION INC
Category: otc | Type: HUMAN OTC DRUG LABEL
Date: 20111021

ACTIVE INGREDIENTS: TRICLOSAN 0.6 mL/100 mL
INACTIVE INGREDIENTS: WATER; SODIUM LAURETH SULFATE; DIPROPYLENE GLYCOL; SODIUM XYLENESULFONATE; COCAMIDOPROPYL BETAINE; POLYSORBATE 20; SODIUM PHOSPHATE, DIBASIC; CITRIC ACID MONOHYDRATE; METHYLCHLOROISOTHIAZOLINONE; METHYLISOTHIAZOLINONE; FD&C RED NO. 4; FD&C YELLOW NO. 5

DRUG FACTS

ACTIVE INGREDIENT

TRICLOSAN 0.6 PERCENT

PURPOSE

ANTIBACTERIAL

USES

HELPS REDUCE BACTERIA ON THE SKIN.

WARNINGS

FOR EXTERNAL USE ONLY.

WHEN USING THIS PRODUCT

AVOID CONTACT WITH EYES.IF CONTACT OCCURS, RINSE WITH WATER.

STOP USING THIS PRODUCT AND ASK DOCTOR IF

IF IRRITATION AND REDNESS DEVELOPS AND LASTS.

KEEP OUT OF REACH OF CHILDREN

IN CASE OF ACCIDENTAL INGESTION, GET MEDICAL HELP OR CONTACT A POISON CONTROL CENTER IMMEDIATELY.

DIRECTIONS

PUMP ONTO DRY HANDS, WORK INTO A LATHER VIGOROUSLY AND RINSE THOROUGHLY.

INACTIVE INGREDIENTS

WATER, SODIUM LAURETH SULFATE, DIPROPYLENE GLYCOL, SODIUM XYLENESULFONATE, COCAMIDOPROPYL BETAINE, POLYSORBATE 20, FRAGRANCE, DISODIUM PHOSPHATE, CITRIC ACID, METHYLCHLOROISOTHIAZOLINONE, METHYLISOTHIAZOLINONE, RED 4 (CI 14700), YELLOW 5 (CI 19140).